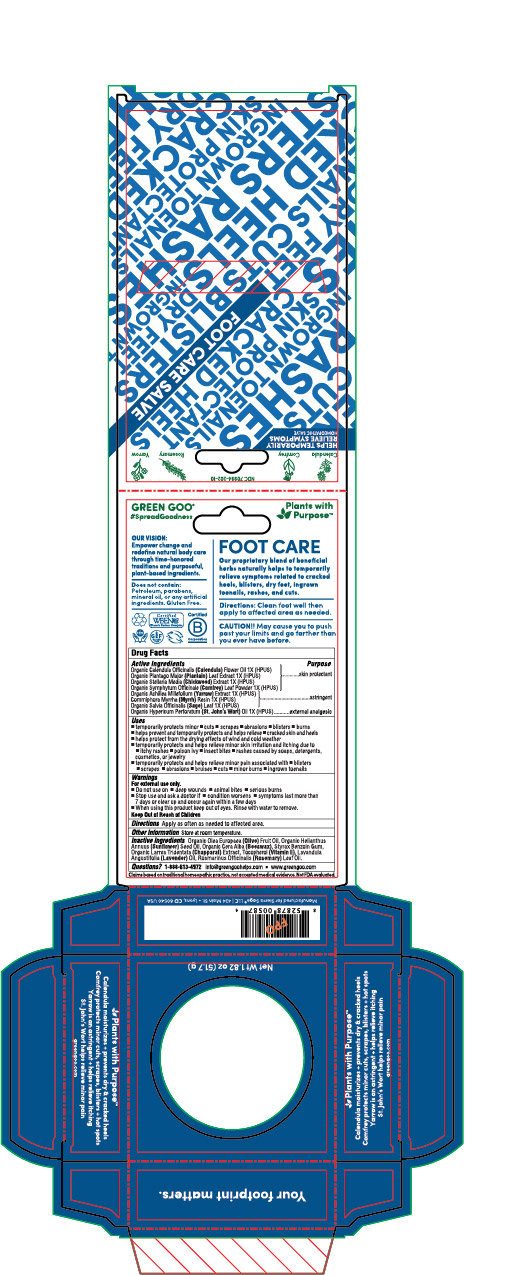 DRUG LABEL: Foot Care
NDC: 70994-202 | Form: SALVE
Manufacturer: Spry Life LLC
Category: homeopathic | Type: HUMAN OTC DRUG LABEL
Date: 20251215

ACTIVE INGREDIENTS: ACHILLEA MILLEFOLIUM FLOWER 1 [hp_X]/51.7 g; ST. JOHN'S WORT 1 [hp_X]/51.7 g; STELLARIA MEDIA 1 [hp_X]/51.7 g; CALENDULA OFFICINALIS FLOWER 1 [hp_X]/51.7 g; PLANTAGO MAJOR 1 [hp_X]/51.7 g; COMMIPHORA MYRRHA WHOLE 1 [hp_X]/51.7 g; SALVIA OFFICINALIS WHOLE 1 [hp_X]/51.7 g; COMFREY LEAF 1 [hp_X]/51.7 g
INACTIVE INGREDIENTS: LARREA TRIDENTATA LEAF; ALPHA-TOCOPHEROL; YELLOW WAX; ROSEMARY OIL; STYRAX BENZOIN RESIN; LAVENDER OIL; OLIVE OIL; SUNFLOWER OIL

Foot Care

Purpose Section

Skin Protectant

Astringent

External Analgesic

Active Ingredients

Organic Calendula Officinalis (Calendula) Flower Oil 1X (HPUS)
Organic Plantago Major (Plantain) Leaf Extract 1X (HPUS)
Organic Stellaria Media (Chickweed) Extract 1X (HPUS)
Organic Symphytum Officinale (Comfrey) Leaf Powder 1X (HPUS)

OrganicAchilleaMillefolium(Yarrow)Extract1X(HPUS)

Commiphora Myrrha (Myrrh) Resin 1X (HPUS)

Organic Salvia Officinalis (Sage) Leaf 1X (HPUS)
Organic Hypericum Perforatum (St. John’s Wort) Oil 1X (HPUS).

Indications & Usage

-temporarily protects minor • cuts • scrapes • abrasions • blisters • burns

-helps prevent and temporarily protects and helps relieve • cracked skin and heels

-helps protect from the drying effects of wind and cold weather

-Temporarily protects and helps relieve minor skin irritation and itching due to • itchy rashes • poison ivy • insect bites • rashes caused by soaps, detergents, cosmetics, or jewelry

-temporarily protects and helps relieve minor pain associated with • blisters • scrapes • abrasions • bruises • cuts • minot burns • ingrown toenails

Keep out of reach of children section

Keep out of reach of children.

Warnings Section

Warnings

For external use only.

- Do not use on • on deep wounds • animal bites • serious burns

- Stop use and ask a doctor if • condition worsens • symptoms last more than 7 days or clear up and occur again within a few days

- When using this product keep out of eyes. Rinse with water to remove.

Storage

Store at room temperature.

Dosage & Administration Section

Apply as often as needed to affected area.

Inactive Ingredients

Organic Olea Europaea (Olive) Fruit Oil, Organic Helianthus Annuus (Sunflower) Seed Oil, Organic Cera Alba (Beeswax), Styrax Benzoin Gum, Organic Larrea Tridentata (Chapparal) Extract, Tocopherol (Vitamin E), Lavandula Angustifolia (Lavender) Oil, Rosmarinus Officinalis (Rosemary) Leaf Oil.